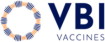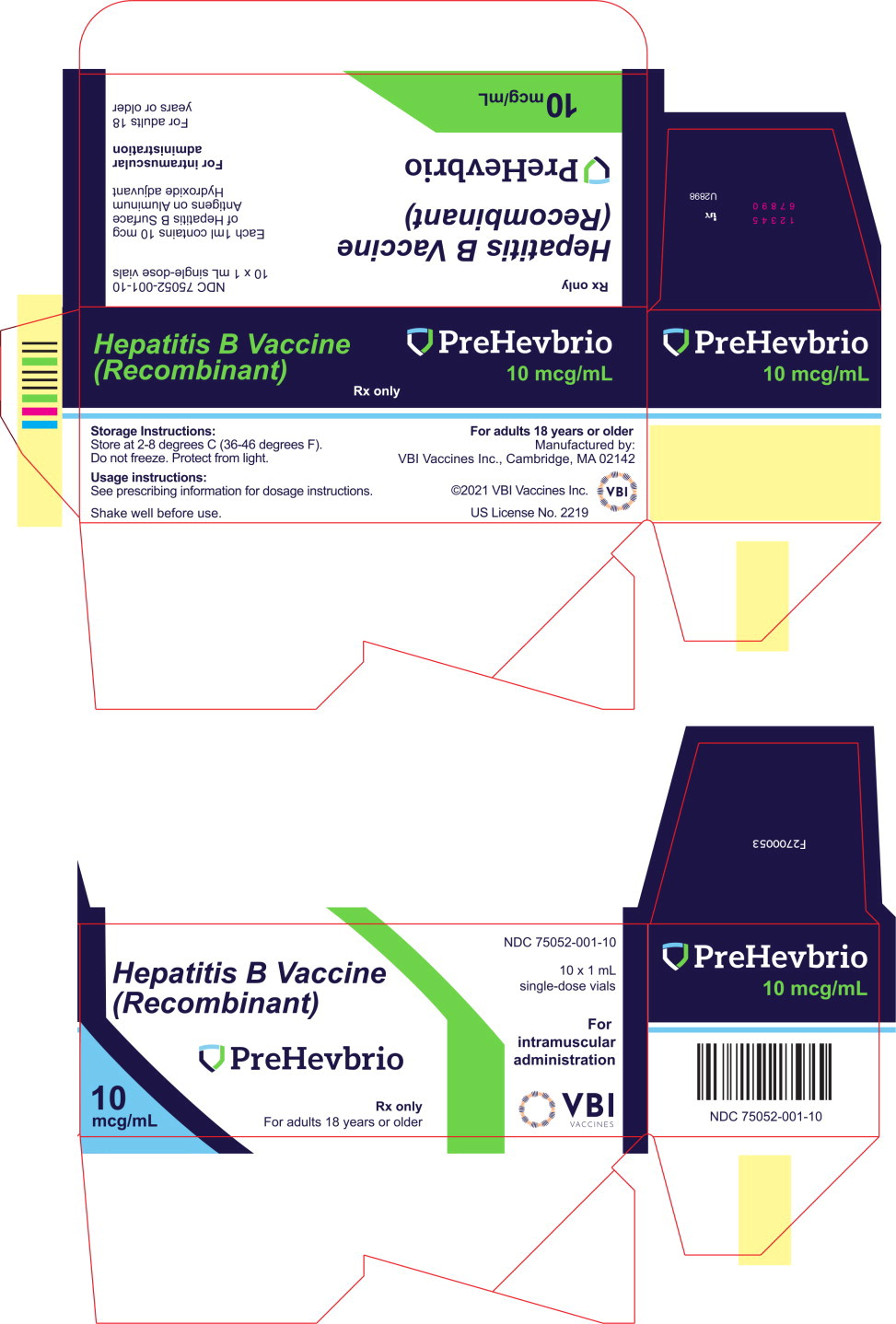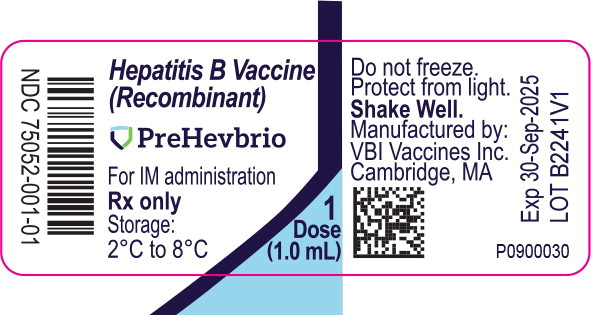 DRUG LABEL: PREHEVBRIO
NDC: 75052-001 | Form: INJECTION, SUSPENSION
Manufacturer: VBI Vaccines (Delaware) Inc.
Category: other | Type: VACCINE LABEL
Date: 20240222

ACTIVE INGREDIENTS: RECOMBINANT HEPATITIS B SURFACE ANTIGEN (ISOFORM S) 10 ug/1 mL; RECOMBINANT HEPATITIS B SURFACE ANTIGEN (ISOFORM M) 1.1 ug/1 mL; RECOMBINANT HEPATITIS B SURFACE ANTIGEN (ISOFORM L) 0.6 ug/1 mL
INACTIVE INGREDIENTS: SODIUM CHLORIDE 8450 ug/1 mL; POTASSIUM CHLORIDE 20 ug/1 mL; SODIUM PHOSPHATE, DIBASIC, DODECAHYDRATE 380 ug/1 mL; MONOBASIC POTASSIUM PHOSPHATE 20 ug/1 mL; SODIUM HYDROXIDE; HYDROCHLORIC ACID; ALUMINUM HYDROXIDE 1500 ug/1 mL; WATER

HIGHLIGHTS OF PRESCRIBING INFORMATION

These highlights do not include all the information needed to use PREHEVBRIOTM safely and effectively. See full prescribing information for PREHEVBRIO.
PREHEVBRIO [Hepatitis B Vaccine (Recombinant)]
Injectable suspension, for intramuscular use
Initial U.S. Approval: 2021

1 INDICATIONS AND USAGE

PREHEVBRIO is indicated for prevention of infection caused by all known subtypes of hepatitis B virus. PREHEVBRIO is approved for use in adults 18 years of age and older. (1)

2 DOSAGE AND ADMINISTRATION

For intramuscular injection.

Administer a series of three doses (1.0 mL each) of PREHEVBRIO on a 0-, 1- and 6-month schedule. (2.1, 2.2)

3 DOSAGE FORMS AND STRENGTHS

PREHEVBRIO is an injectable suspension, for intramuscular use supplied as a single-dose vial. A single dose of PREHEVBRIO is 1.0 mL (3)

4 CONTRAINDICATIONS

Severe allergic reaction (e.g., anaphylaxis) after a previous dose of any hepatitis B vaccine or to any component of PREHEVBRIO. (4)

6 ADVERSE REACTIONS

Individuals 18 through 44 years of age: The most common local reactions following each dose of PREHEVBRIO were injection site pain (52.0 – 58.3%) and tenderness (52.6 – 59.6%). The most common systemic reactions following each dose of PREHEVBRIO were headache (17.2 – 25.8%), fatigue (20.1- 28.3%) and myalgia (22.2 – 29.9%).

Individuals 45 through 64 years of age: The most common local reactions following each dose of PREHEVBRIO were injection site pain (42.2 – 48.8%) and tenderness (43.2 – 50.5%). The most common systemic reactions following each dose of PREHEVBRIO were headache (13.8 – 21.3%), fatigue (14.3 – 19.7%) and myalgia (16.7 – 24.1%).

Individuals ≥ 65 years of age: The most common local reactions following each dose of PREHEVBRIO were injection site pain (26.7 – 34.8%) and tenderness (30.2 – 32.8%). The most common systemic reactions following each dose of PREHEVBRIO were headache (7.3 – 12.2%), fatigue (11.5 – 14.5%) and myalgia (11.5 - 16.6%). (6.1)

To report SUSPECTED ADVERSE REACTIONS, contact VBI Vaccines at 1-888-421-8808 (toll-free) or VAERS at 1-800-822-7967 or www.vaers.hhs.gov .

FULL PRESCRIBING INFORMATION

1 INDICATIONS AND USAGE

PREHEVBRIO is indicated for prevention of infection caused by all known subtypes of hepatitis B virus.

PREHEVBRIO is approved for use in adults 18 years of age and older.

2 DOSAGE AND ADMINISTRATION

For intramuscular injection.

2.1 Dosage and Schedule

Administer a series of three doses (1.0 mL each) of PREHEVBRIO on a 0-, 1- and 6-month schedule.

2.2 Administration

Shake the vial of PREHEVBRIO well to obtain a slightly opaque, white suspension.

Parenteral drug products should be inspected visually for particulate matter and discoloration prior to administration whenever solution and container permit. If either of these conditions exists, the vaccine should not be administered.

Administer PREHEVBRIO by intramuscular injection.

3 DOSAGE FORMS AND STRENGTHS

PREHEVBRIO is an injectable suspension, for intramuscular use supplied as a single-dose vial. A single dose of PREHEVBRIO is 1.0 mL [see How Supplied/Storage and Handling (16.1)].

4 CONTRAINDICATIONS

Do not administer PREHEVBRIO to individuals with a history of severe allergic reaction (e.g., anaphylaxis) after a previous dose of any hepatitis B vaccine or to any component of PREHEVBRIO [see Description (11)].

5 WARNINGS AND PRECAUTIONS

5.1 Managing Allergic Reactions

Appropriate medical treatment and supervision must be available to manage possible anaphylactic reactions following administration of PREHEVBRIO.

5.2 Immunocompromised Individuals

Immunocompromised persons, including individuals receiving immunosuppressant therapy, may have a diminished immune response to PREHEVBRIO.

5.3 Limitations of Vaccine Effectiveness

Hepatitis B has a long incubation period. PREHEVBRIO may not prevent hepatitis B infection in individuals who have an unrecognized hepatitis B infection at the time of vaccine administration.

6 ADVERSE REACTIONS

Individuals 18 through 44 years of age: The most common local reactions following each dose of PREHEVBRIO were injection site pain (52.0 – 58.3%) and tenderness (52.6 – 59.6%). The most common systemic reactions following each dose of PREHEVBRIO were headache (17.2 – 25.8%), fatigue (20.1- 28.3%) and myalgia (22.2 – 29.9%).

Individuals 45 through 64 years of age: The most common local reactions following each dose of PREHEVBRIO were injection site pain (42.2 – 48.8%) and tenderness (43.2 – 50.5%). The most common systemic reactions following each dose of PREHEVBRIO were headache (13.8 – 21.3%), fatigue (14.3 – 19.7%) and myalgia (16.7 – 24.1%).

Individuals ≥ 65 years of age: The most common local reactions following each dose of PREHEVBRIO were injection site pain (26.7 – 34.8%) and tenderness (30.2 – 32.8%). The most common systemic reactions following each dose of PREHEVBRIO were headache (7.3 – 12.2%), fatigue (11.5 – 14.5%) and myalgia (11.5 - 16.6%).

6.1 Clinical Trials Experience

Because clinical trials are conducted under widely varying conditions, adverse reaction rates observed in the clinical trials of a vaccine cannot be directly compared to rates in the clinical trials of another vaccine and may not reflect the rates observed in practice.

The safety of PREHEVBRIO was evaluated in 2 active-controlled clinical studies (Studies 1 and 2) involving 4,443 subjects who received at least 1 dose of PREHEVBRIO (n = 2,920) or Engerix-B [Hepatitis B Vaccine (Recombinant)] (n = 1,523) administered according to a 0-, 1- and 6-months schedule.

Study 1 in adults ≥18 years of age

Study 1 was a randomized, double-blind, active-controlled, multicenter study that enrolled subjects in the United States (US), Canada, Belgium and Finland in which 796 subjects received at least 1 dose of PREHEVBRIO and 811 subjects received at least 1 dose of Engerix-B. In the total study population at baseline the mean age was 57 years, 81% were age ≥45 years; 62% were women; 90% were White, 8% Black, 1% Asian, and 10% Hispanic/Latino; 37% were obese (body mass index [BMI] >30 kg/m^2), 14% were current smokers and 8% had Type 2 diabetes mellitus. Demographic and baseline characteristics were similar in both vaccine groups.

Solicited Local and Systemic Adverse Reactions

Subjects were monitored for local and systemic adverse reactions using diary cards for a 7-day period starting on the day of vaccination. The percentages of subjects who reported local and systemic reactions in Study 1 are shown by age subgroup in Table 1 to Table 3.

Table 1: Study 1: Percent of Subjects Who Reported Local or Systemic Reactions Within 7 Days of Vaccination (18 through 44 years of age)
 | PREHEVBRIO Dose 1 (N=145) % | PREHEVBRIO Dose 2 (N=141) % | PREHEVBRIO Dose 3 (N= 134) % | Engerix-B Dose 1 (N=154) % | Engerix-B Dose 2 (N=152) % | Engerix-B Dose 3 (N=148) %
Local Reaction
Pain | 58.6 | 50.4 | 46.3 | 33.8 | 28.9 | 31.8
Pain, Grade 3 or greatera | 0 | 0 | 0 | 0 | 0 | 0
Tenderness | 53.8 | 50.4 | 42.5 | 32.5 | 32.2 | 36.5
Tenderness, Grade 3 or greaterb | 0.7 | 0 | 0.7 | 0.6 | 0.7 | 0.7
Itching | 2.1 | 3.5 | 6.0 | 7.1 | 3.9 | 7.4
Itching, Grade 3 or greaterc | 0 | 0 | 0 | 0 | 0.7 | 1.4
Redness (≥ 2.5 cm) | 0.7 | 1.4 | 1.5 | 0.6 | 1.3 | 0
Redness, Grade 3 or greaterd | 0 | 0 | 0 | 0 | 0 | 0
Swelling (≥ 2.5 cm) | 2.8 | 1.4 | 0.7 | 0 | 1.3 | 2.0
Swelling, Grade 3 or greatere | 0 | 0 | 0 | 0 | 0.7 | 1.4
Systemic Reaction
Headache | 33.8 | 24.1 | 20.9 | 29.9 | 19.1 | 13.5
Headache, Grade 3 or greatera | 1.4 | 0.7 | 0 | 1.3 | 0.7 | 0
Fatigue | 29.7 | 22.0 | 22.4 | 31.8 | 20.4 | 20.3
Fatigue, Grade 3 or greaterc | 1.4 | 0.7 | 0 | 0.6 | 2.0 | 1.4
Myalgia | 27.6 | 24.1 | 21.6 | 20.8 | 11.8 | 10.1
Myalgia, Grade 3 or greaterc | 0.7 | 0 | 0 | 0 | 1.3 | 0
Diarrhea | 9.7 | 5.7 | 4.5 | 9.7 | 5.9 | 7.4
Diarrhea, Grade 3 or greaterf | 0.7 | 0 | 0 | 0 | 0.7 | 0
Nausea/Vomiting | 8.3 | 4.3 | 4.5 | 7.8 | 6.6 | 6.1
Nausea/Vomiting, Grade 3 or greaterf | 0 | 0.7 | 0 | 0 | 0.7 | 0
Fever (≥100.4°F) | 0.7 | 0.7 | 0 | 1.3 | 0 | 0.7
Fever, Grade 3 or greater (≥102.1°F) | 0.7 | 0 | 0 | 0 | 0 | 0
a Grade 3 or greater pain and headache: defined as use of narcotic pain reliever or prevents daily activity; or ER visit or hospitalization
b Grade 3 or greater tenderness: defined as significant discomfort at rest; or ER visit or hospitalization
c Grade 3 or greater itching, fatigue and myalgia: defined as prevents daily activity; or ER visit or hospitalization
d Grade 3 or greater redness: defined as > 10 cm or skin necrosis or exfoliative dermatitis
e Grade 3 or greater swelling: defined as > 10 cm or prevents daily activity; or skin necrosis.
f Grade 3 or greater diarrhea and nausea/vomiting: defined as prevents daily activity or requires outpatient IV hydration; or ER visit or hospitalization.

Table 2: Study 1: Percent of Subjects Who Reported Local or Systemic Reactions Within 7 Days of Vaccination (45 through 64 years of age)
 | PREHEVBRIO Dose 1 (N=355) % | PREHEVBRIO Dose 2 (N=350) % | PREHEVBRIO Dose 3 (N=343) % | Engerix-B Dose 1 (N=361) % | Engerix-B Dose 2 (N=357) % | Engerix-B Dose 3 (N=349) %
Local Reaction
Pain | 46.8 | 44.9 | 39.4 | 22.2 | 15.4 | 17.2
Pain, Grade 3 or greatera | 0 | 0 | 0.3 | 0 | 0 | 0
Tenderness | 48.7 | 42.6 | 40.5 | 23.8 | 16.5 | 17.5
Tenderness, Grade 3 or greaterb | 0.8 | 0.6 | 0.3 | 0 | 0 | 0.3
Itching | 4.5 | 3.1 | 3.8 | 3.9 | 2.0 | 3.4
Itching, Grade 3 or greaterc | 0 | 0.3 | 0 | 0 | 0 | 0
Redness (≥ 2.5 cm) | 1.7 | 0.6 | 0.3 | 1.1 | 0.3 | 1.1
Redness, Grade 3 or greaterd | 0 | 0 | 0 | 0.8 | 0.3 | 0.6
Swelling (≥ 2.5 cm) | 1.4 | 0.3 | 0.9 | 0 | 0.6 | 0.3
Swelling, Grade 3 or greatere | 0 | 0 | 0.3 | 0 | 0 | 0
Systemic Reaction
Headache | 21.4 | 13.7 | 15.7 | 20.5 | 11.2 | 14.0
Headache, Grade 3 or greatera | 0 | 0 | 0.3 | 0.3 | 0.3 | 0.3
Fatigue | 16.6 | 16.9 | 12.5 | 22.2 | 11.5 | 12.3
Fatigue, Grade 3 or greaterc | 0.6 | 0 | 0.3 | 0.6 | 0.3 | 0.6
Myalgia | 21.4 | 20.0 | 15.5 | 16.1 | 8.4 | 9.5
Myalgia, Grade 3 or greaterc | 0.6 | 0 | 0 | 0 | 0 | 0
Diarrhea | 4.8 | 4.0 | 3.2 | 6.4 | 3.6 | 3.7
Diarrhea, Grade 3 or greaterf | 0 | 0 | 0 | 0 | 0 | 0
Nausea/Vomiting | 4.2 | 2.9 | 2.3 | 6.4 | 3.6 | 2.6
Nausea/Vomiting, Grade 3 or greaterf | 0 | 0 | 0 | 0 | 0 | 0
Fever (≥100.4°F) | 0.6 | 0 | 0 | 0.3 | 0.3 | 0.6
Fever, Grade 3 or greater (≥102.1°F) | 0 | 0 | 0 | 0 | 0 | 0.3
a Grade 3 or greater pain and headache: defined as use of narcotic pain reliever or prevents daily activity; or ER visit or hospitalization
b Grade 3 or greater tenderness: defined as significant discomfort at rest; or ER visit or hospitalization
c Grade 3 or greater itching, fatigue and myalgia: defined as prevents daily activity; or ER visit or hospitalization
d Grade 3 or greater redness: defined as > 10 cm or skin necrosis or exfoliative dermatitis
e Grade 3 or greater swelling: defined as > 10 cm or prevents daily activity; or skin necrosis.
f Grade 3 or greater diarrhea and nausea/vomiting: defined as prevents daily activity or requires outpatient IV hydration; or ER visit or hospitalization.

Table 3: Study 1: Percent of Subjects Who Reported Local or Systemic Reactions Within 7 Days of Vaccination (≥ 65 years of age)
 | PREHEVBRIO Dose 1 (N=296) % | PREHEVBRIO Dose 2 (N=288) % | PREHEVBRIO Dose 3 (N=281) % | Engerix-B Dose 1 (N=296) % | Engerix-B Dose 2 (N=292) % | Engerix-B Dose 3 (N= 288) %
Local Reaction
Pain | 34.8 | 28.8 | 26.7 | 16.2 | 12.0 | 11.1
Pain, Grade 3 or greatera | 0 | 0 | 0 | 0.3 | 0 | 0
Tenderness | 32.8 | 30.2 | 31.0 | 14.2 | 12.0 | 10.1
Tenderness, Grade 3 or greaterb | 0 | 0 | 0 | 0 | 0 | 0
Itching | 6.1 | 3.8 | 5.0 | 4.1 | 1.4 | 2.4
Itching, Grade 3 or greaterc | 0 | 0 | 0 | 0 | 0 | 0
Redness (≥ 2.5 cm) | 1.0 | 0.3 | 1.4 | 0.7 | 0.3 | 0
Redness, Grade 3 or greaterd | 0.3 | 0 | 0.4 | 0 | 0.3 | 0
Swelling (≥ 2.5 cm) | 1.0 | 0.7 | 1.1 | 1.4 | 0.3 | 0.3
Swelling, Grade 3 or greatere | 0.3 | 0 | 0 | 0 | 0.3 | 0
Systemic Reaction
Headache | 12.2 | 7.3 | 7.8 | 12.8 | 5.8 | 6.9
Headache, Grade 3 or greatera | 0 | 0 | 0 | 0 | 0 | 0
Fatigue | 14.5 | 11.5 | 12.5 | 17.9 | 9.9 | 10.1
Fatigue, Grade 3 or greaterc | 0 | 0 | 0 | 0.7 | 0 | 0.3
Myalgia | 16.6 | 11.5 | 13.2 | 12.8 | 8.2 | 6.9
Myalgia, Grade 3 or greaterc | 0 | 0 | 0 | 0 | 0.3 | 0
Diarrhea | 6.4 | 4.2 | 1.1 | 6.4 | 2.4 | 3.5
Diarrhea, Grade 3 or greaterf | 0.3 | 0 | 0 | 0.3 | 0 | 0
Nausea/Vomiting | 3.7 | 0.7 | 1.1 | 1.7 | 1.7 | 0.7
Nausea/Vomiting, Grade 3 or greaterf | 0 | 0 | 0 | 0.3 | 0 | 0.3
Fever (≥100.4°F) | 0 | 0 | 0.7 | 0 | 0 | 0.7
Fever, Grade 3 or greater (≥102.1°F) | 0 | 0 | 0 | 0 | 0 | 0
a Grade 3 or greater pain and headache: defined as use of narcotic pain reliever or prevents daily activity; or ER visit or hospitalization
b Grade 3 or greater tenderness: defined as significant discomfort at rest; or ER visit or hospitalization
c Grade 3 or greater itching, fatigue and myalgia: defined as prevents daily activity; or ER visit or hospitalization
d Grade 3 or greater redness: defined as > 10 cm or skin necrosis or exfoliative dermatitis
e Grade 3 or greater swelling: defined as > 10 cm or prevents daily activity; or skin necrosis.
f Grade 3 or greater diarrhea and nausea/vomiting: defined as prevents daily activity or requires outpatient IV hydration; or ER visit or hospitalization.

The median duration of local and systemic solicited adverse reactions was 1-2 days in both treatment groups. Among all subjects who received PREHEVBRIO, the frequencies of the most commonly reported solicited reactions extending beyond the 7-day assessment period were as follows: fatigue (4.1%), injection site pain (2.0%), headache (1.9%) and myalgia (1.9%).

Study 2 in adults 18 through 45 years of age

Study 2 was a randomized, double-blind, active-controlled, multicenter study that enrolled subjects in the US, Canada, Belgium, Finland, Germany and the United Kingdom in which 2,124 subjects received at least 1 dose of PREHEVBRIO and 712 subjects received at least 1 dose of Engerix-B. In the total study population at baseline, the mean age was 34 years; 58% were women; 92% were White, 6% Black, 2% Asian, and 10% Hispanic/Latino; 18% were obese (BMI >30 kg/m^2) and 19% were current smokers. Demographic and baseline characteristics were similar in both vaccine groups.

Solicited Local and Systemic Adverse Reactions

Subjects were monitored for local and systemic adverse reactions using diary cards for a 7-day period starting on the day of vaccination. The percentages of subjects who reported local and systemic reactions in Study 2 are shown in Table 4.

Table 4: Study 2: Percent of Subjects Who Reported Local or Systemic Reactions Within 7 Days of Vaccination (18 through 45 years of age)
 | PREHEVBRIO Dose 1 (N=2122) a % | PREHEVBRIO Dose 2 (N=2071) % | PREHEVBRIO Dose 3 (N=1967) % | Engerix-B Dose 1 (N=712) % | Engerix-B Dose 2 (N=701) % | Engerix-B Dose 3 (N=671) %
Local Reaction
Pain | 58.2 | 52.2 | 52.5 | 35.1 | 29.2 | 32.5
Pain, Grade 3 or greaterb | 0.3 | 0.3 | 0.4 | 0.1 | 0 | 0.3
Tenderness | 59.9 | 52.9 | 55.5 | 37.6 | 30.4 | 33.8
Tenderness, Grade 3 or greaterc | 0.8 | 0.9 | 0.8 | 0.6 | 0.1 | 0.1
Itching | 5.7 | 5.7 | 6.7 | 6.6 | 5.3 | 5.4
Itching, Grade 3 or greaterd | 0 | 0 | 0.1 | 0.3 | 0.1 | 0
Redness (≥ 2.5 cm) | 1.1 | 1.1 | 1.3 | 0.6 | 0.4 | 1.0
Redness, Grade 3 or greatere | 0.2 | 0 | 0.2 | 0.1 | 0.1 | 0.1
Swelling (≥ 2.5 cm) | 1.2 | 0.9 | 1.1 | 0.6 | 0 | 0.4
Swelling, Grade 3 or greaterf | 0.1 | 0 | 0.1 | 0 | 0 | 0
Systemic Reaction
Headache | 25.1 | 16.7 | 17.4 | 24.2 | 15.0 | 18.3
Headache, Grade 3 or greaterb | 0.3 | 0.2 | 0.5 | 0.4 | 0.4 | 0.6
Fatigue | 28.4 | 19.8 | 20.2 | 27.1 | 17.8 | 22.1
Fatigue, Grade 3 or greaterd | 0.5 | 0.8 | 0.6 | 0.4 | 0.6 | 0.6
Myalgia | 30.3 | 21.9 | 23.6 | 17.7 | 13.0 | 18.5
Myalgia, Grade 3 or greaterd | 0.3 | 0.6 | 0.5 | 0.4 | 0.1 | 0.4
Diarrhea | 7.4 | 5.0 | 4.4 | 9.6 | 4.9 | 5.4
Diarrhea, Grade 3 or greaterg | 0.2 | 0.1 | 0.1 | 0 | 0 | 0
Nausea/Vomiting | 6.7 | 3.7 | 4.7 | 7.0 | 3.6 | 3.9
Nausea/Vomiting, Grade 3 or greaterg | 0 | 0 | 0.2 | 0 | 0.1 | 0
Fever (≥100.4°F) | 0.3 | 0.3 | 0.6 | 0.4 | 0.3 | 0.9
Fever, Grade 3 or greater (≥102.1°F) | 0 | 0.1 | 0.1 | 0.1 | 0 | 0
a Two subjects without solicited adverse event data following dose 1 of PREHEVBRIO were excluded from this analysis.
b Grade 3 or greater pain and headache: defined as use of narcotic pain reliever or prevents daily activity; or ER visit or hospitalization
c Grade 3 or greater tenderness: defined as significant discomfort at rest; or ER visit or hospitalization
d Grade 3 or greater itching, fatigue and myalgia: defined as prevents daily activity; or ER visit or hospitalization
e Grade 3 or greater redness: defined as > 10 cm or skin necrosis or exfoliative dermatitis
f Grade 3 or greater swelling: defined as > 10 cm or prevents daily activity; or skin necrosis
g Grade 3 or greater diarrhea and nausea/vomiting: defined as prevents daily activity or requires outpatient IV hydration; or ER visit or hospitalization.

The median duration of local and systemic solicited adverse reactions was 1-2 days in both treatment groups. Among all subjects who received PREHEVBRIO, the frequencies of the most commonly reported solicited reactions extending beyond the 7-day assessment period were as follows: fatigue (3.5%), injection site pain (2.0%), headache (1.9%) and myalgia (1.8%).

Unsolicited Adverse Events (AEs)

In both studies, unsolicited adverse events, including serious and non-serious events, that occurred within 28 days following each vaccination were recorded on a diary card by all subjects.

In both studies combined, unsolicited AEs that occurred within 28 days of any vaccination were reported by 48.3% and 48.4% of subjects who received PREHEVBRIO or Engerix-B, respectively. Unsolicited AEs in subjects who received PREHEVBRIO for which available information suggests a causal relationship to vaccination include injection site bruising (1.4%), dizziness/vertigo (1.1%), general pruritus/itchiness (0.2%), arthralgia (0.2%), urticaria/hives (0.2%) and lymphadenopathy/lymph node pain (0.1%).

Serious Adverse Events (SAEs)

In both studies, SAEs were collected from first vaccination through 6 months following the last vaccination. In both studies combined, SAEs were reported by 0.9% and 0.6% within 28 days of vaccination with PREHEVBRIO or Engerix-B, respectively. SAEs were reported by 2.5% of subjects in the PREHEVBRIO group and 1.6% in the Engerix-B group from the first vaccination through 6 months following the third vaccination. There were no notable patterns or numerical imbalances between vaccination groups for specific categories of serious adverse events that would suggest a causal relationship to PREHEVBRIO.

7 DRUG INTERACTIONS

7.1 Concomitant Administration with Immune Globulin

There are no data to assess the concomitant use of PREHEVBRIO with immune globulin. When concomitant administration of PREHEVBRIO and immune globulin is required, they should be given with different syringes at different injection sites.

7.2 Interference with Laboratory Tests

Hepatitis B surface antigen (HBsAg) derived from hepatitis B vaccines has been transiently detected in blood samples following vaccination. Serum HBsAg detection may not have diagnostic value within 28 days after receipt of PREHEVBRIO.

8 USE IN SPECIFIC POPULATIONS

8.1 Pregnancy

Pregnancy Exposure Registry

There is a pregnancy exposure registry that monitors pregnancy outcomes in women exposed to PREHEVBRIO during pregnancy. Women who receive PREHEVBRIO during pregnancy are encouraged to contact 1-888-421-8808 (toll-free).

Risk Summary

All pregnancies have a risk of birth defect, loss, or other adverse outcomes. In clinically recognized pregnancies in the US general population, the estimated background risk of major birth defects is 2% to 4% and of miscarriage is 15% to 20%.

There are no adequate and well-controlled studies of PREHEVBRIO in pregnant women. Available human data on PREHEVBRIO administered to pregnant women are insufficient to inform vaccine-associated risks in pregnancy.

A developmental toxicity study has been performed in female rats administered the equivalent of a single human dose of PREHEVBRIO on four occasions; twice prior to mating, twice during gestation. The study revealed no evidence of harm to the fetus due to the vaccine [see Animal Data below].

Data

Animal Data

A developmental toxicity study has been performed in female rats using a dose equivalent to the adult human dose. In the study, female rats received 0.5 mL (2 x 0.25 mL injections) of a vaccine formulation containing 10 mcg HBsAg (S, pre-S1, pre-S2) adsorbed on to aluminum hydroxide by intramuscular injection 30 days and 15 days prior to mating and on gestation days 4 and 15. No adverse effects of pre-weaning development were observed. There was no evidence of fetal malformations or variations.

8.2 Lactation

Risk Summary

It is not known whether PREHEVBRIO is excreted in human milk. Data are not available to assess the effects of PREHEVBRIO on the breastfed infant or on milk production/excretion.

The developmental and health benefits of breastfeeding should be considered along with the mother's clinical need for PREHEVBRIO and any potential adverse effects on the breastfed child from PREHEVBRIO or from the underlying maternal condition. For preventive vaccines, the underlying condition is susceptibility to disease prevented by the vaccine.

8.4 Pediatric Use

Safety and effectiveness of PREHEVBRIO have not been established in individuals less than 18 years of age.

8.5 Geriatric Use

Study 1 included 296 adults 65 through 86 years of age who received PREHEVBRIO. Among subjects who received PREHEVBRIO, a seroprotective level of antibody to HBsAg was achieved in 83.6% of those ≥ 65 years of age compared to 94.8% in adults 45 through 64 years of age and 99.2% in adults 18 through 44 years of age [see Evaluation of Immunogenicity (14.1)].

Frequencies of local and systemic solicited adverse reactions were generally lower in elderly subjects ≥65 years of age than in younger subjects [see Adverse Reactions (6)].

8.6 Adults on Hemodialysis

Safety and effectiveness of PREHEVBRIO have not been established in adults on hemodialysis.

11 DESCRIPTION

PREHEVBRIO [Hepatitis B Vaccine (Recombinant)] is a sterile suspension for intramuscular injection.

PREHEVBRIO contains the small (S), middle (pre-S2) and large (pre-S1) hepatitis B surface antigens, co-purified from genetically modified CHO (Chinese Hamster Ovary) cells cultured in growth medium containing vitamins, amino acids, minerals, and fetal bovine serum.

The hepatitis B surface antigens are co-purified from the supernatant of CHO cells by a series of physicochemical steps as virus-like particles containing CHO cell membrane lipids.

Each 1.0 mL dose is formulated to contain 10 mcg hepatitis B surface antigens (S, pre-S1 and pre-S2) adsorbed on aluminum hydroxide [Al(OH)3] as an adjuvant (aluminum content of 0.5 mg/mL).

Each 1.0 mL dose of PREHEVBRIO also contains sodium chloride (NaCl) (8.45 mg/dose), potassium chloride (KCl) (0.02 mg/dose), disodium hydrogen phosphate dodecahydrate (Na2HPO4.12H2O) (0.38 mg/dose), potassium dihydrogen phosphate anhydrous (KH2PO4) (0.02 mg/dose) and water for injections (WFI). Each dose may contain residual amounts of CHO cell proteins (up to 2.5 ng/dose), CHO cell DNA (up to 10 pg/dose), Bovine Serum Albumin (up to 2.5 ng/dose) and Formaldehyde (up to 500 ng/dose) from the manufacturing process.

PREHEVBRIO does not contain a preservative.

The vial stoppers are not made with natural rubber latex.

12 CLINICAL PHARMACOLOGY

12.1 Mechanism of Action

PREHEVBRIO induces antibodies to HBsAg. Antibody concentrations ≥10 mIU/mL against HBsAg are recognized as conferring protection against hepatitis B virus infection.

13 NONCLINICAL TOXICOLOGY

13.1 Carcinogenesis, Mutagenesis, Impairment of Fertility

PREHEVBRIO has not been evaluated for carcinogenic, mutagenic potential or male infertility in animals. In a developmental toxicity study in rats with a vaccine formulation containing 10 mcg HBsAg (S, pre-S1, pre-S2) adsorbed on to aluminum hydroxide there were no effects on female fertility [see Animal Data (8.1)].

14 CLINICAL STUDIES

14.1 Evaluation of Immunogenicity

The immunogenicity of PREHEVBRIO was evaluated in comparison with a US-licensed hepatitis B vaccine (Engerix-B) in 2 randomized, active controlled, double-blind, multi-center Phase 3 clinical trials in adults. PREHEVBRIO and Engerix-B were administered according to a 0-, 1- and 6-month schedule. For subject baseline characteristics, see section 6.1.

The trials compared the seroprotection rates (SPR), defined as the proportion of participants with anti-HBs titers ≥ 10 mIU/mL, induced by PREHEVBRIO and Engerix-B. Non-inferiority was met if the lower bound of the 95% confidence interval (CI) of the difference in SPR (PREHEVBRIO minus Engerix-B) was greater than -5%.

Study 1 in adults ≥18 years of age

The immunogenicity population included 718 subjects who received PREHEVBRIO and 723 subjects who received Engerix-B. The mean age was 57 years in both groups. The primary analysis compared the SPR, 4 weeks after receiving the third dose of PREHEVBRIO or Engerix-B in subjects ≥ 18 years of age. The SPR induced by PREHEVBRIO compared to Engerix-B was non-inferior in subjects ≥ 18 years of age (Table 5).

Table 5: Study 1: Seroprotection Rate (SPR) 4 Weeks After Receiving the Third Dose of PREHEVBRIO or Engerix-B
Study Population | PREHEVBRIO N | PREHEVBRIO SPR (95% CI) | Engerix-B N | Engerix-B SPR (95% CI) | Difference in SPR; PREHEVBRIO – Engerix-B (95% CI)
All Adults (Age 18+)a | 718 | 91.4 (89.1, 93.3) | 723 | 76.5 (73.2, 79.5) | 14.9 (11.2, 18.6)c
Age 45+b | 625 | 89.4 (86.8, 91.7) | 627 | 73.1 (69.4, 76.5) | 16.4 (12.2, 20.7)d
Age 18-44 | 125 | 99.2 (95.6, 100.0) | 135 | 91.1 (85.0. 95.3) | -e
Age 45-64 | 325 | 94.8 (91.8, 96.6) | 322 | 80.1 (75.3, 84.3) | -e
Age 65 + | 268 | 83.6 (78.6, 87.8) | 266 | 64.7 (58.6, 70.4) | -e
Abbreviations: N=number of subjects in the analysis set; SPR= Seroprotection Rate (percent of subjects with anti-HBs titers ≥10 mIU/mL)
a Per-protocol set (PPS). PPS included all subjects in the full analysis set who received all 3 vaccinations, had an evaluable serum immunogenicity sample at baseline and at the time point of interest, were seronegative at baseline, and had no major protocol violations leading to exclusion.
b Full analysis set (FAS). FAS included all subjects who received at least 1 vaccination and provided at least 1 evaluable serum immunogenicity sample both at baseline and after baseline. Subjects were seronegative at baseline.
c Non-inferiority was met because the lower bound of the 95% CI of the difference in SPR (PREHEVBRIO - Engerix-B) was > -5%.
d The SPR following PREHEVBRIO was statistically significantly higher than following Engerix-B (lower bound of the 95% CI of the difference in SPR was > 0%).
e Exploratory analysis

Study 2 in adults 18 through 45 years of age

The immunogenicity population included 1,753 subjects who received PREHEVBRIO and 592 subjects who received Engerix-B. The mean age was 34 years in the PREHEVBRIO group and 33 years in the Engerix-B group. The study compared the SPR, 4 weeks after receiving the third dose of PREHEVBRIO or Engerix-B in all subjects. The SPR induced by PREHEVBRIO compared to Engerix-B was non-inferior (Table 6).

Table 6: Study 2: Seroprotection Rate (SPR) 4 Weeks After Receiving the Third Dose of PREHEVBRIO or Engerix-B
Study Population | PREHEVBRIO N | PREHEVBRIO SPR (95% CI) | Engerix-B N | Engerix-B SPR (95% CI) | Difference in SPR; PREHEVBRIO –Engerix-B (95% CI)
Age 18-45 | 1753 | 99.3 (98.7. 99.6) | 592 | 94.8 (92.7, 96.4) | 4.5 (2.9, 6.6) *
SPR= Seroprotection Rate (percent of subjects with anti-HBs titers ≥10 mIU/mL)
*Non-inferiority was met because the lower bound of the 95% CI of the difference in SPR (PREHEVBRIO - Engerix-B) was > -5%.

16 HOW SUPPLIED/STORAGE AND HANDLING

16.1 How Supplied

Single dose vial, 1.0 mL (NDC number 75052-001-01)

Supplied as a package of 10 single dose vials (NDC number: 75052-001-10)

The vial stoppers are not made with natural rubber latex.

16.2 Storage Conditions

Store in a refrigerator at 2°C to 8°C (36°F to 46°F). Protect from light.

Do not freeze; discard if the vaccine has been frozen.

Do not use the vaccine after the expiration date shown on the vial label.

17 PATIENT COUNSELING INFORMATION

- Inform vaccine recipient of the potential benefits and risks associated with vaccination with PREHEVBRIO, as well as the importance of completing the immunization series.
- Emphasize that PREHEVBRIO contains non-infectious purified HBsAg and cannot cause hepatitis B infection.
- Advise vaccine recipient to report any adverse events to their healthcare provider or to the Vaccine Adverse Event Reporting System (VAERS) at 1-800-822-7967 and www.vaers.hhs.gov.
- Provide the Vaccine Information Statements, which are available free of charge at the Centers for Disease Control and Prevention (CDC) website (www.cdc.gov/vaccines).

Manufactured by: VBI Vaccines Inc.
160 Second St., 3rd Floor, Cambridge, MA, USA, 02142
U.S. License No. 2219
©2021 VBI Vaccines. All rights reserved.

Principal Display Panel - 10 mcg/mL Carton Label

NDC 75052-001-10

Hepatitis B Vaccine
(Recombinant)

PreHevbrio

Rx only

For adults 18 years or older

10
mcg/mL

10 x 1 mL
single-dose vials

For
intramuscular
administration

VBI
VACCINES

Principal Display Panel - 10 mcg/mL Vial Label

NDC 75052-001-01

Hepatitis B Vaccine
(Recombinant)

PreHevbrio

For IM administration

Rx only

Storage:
2°C to 8°C

1
Dose
(1 mL)